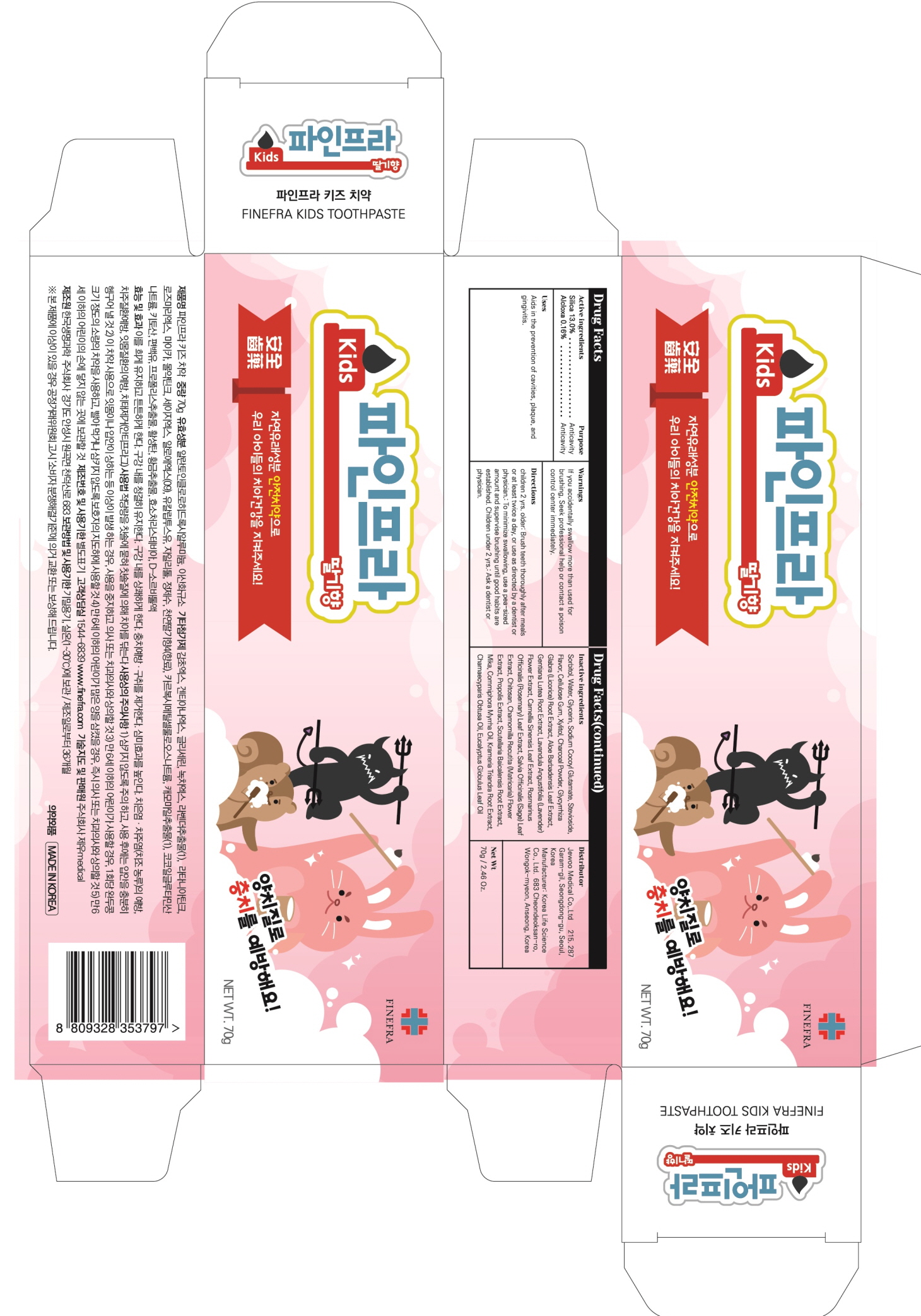 DRUG LABEL: Finefra Kids Tooth
NDC: 69653-120 | Form: PASTE, DENTIFRICE
Manufacturer: Jewoo Medical Co,.Ltd
Category: otc | Type: HUMAN OTC DRUG LABEL
Date: 20191226

ACTIVE INGREDIENTS: SILICON DIOXIDE 9.10 g/70 g; ALCLOXA 0.11 g/70 g
INACTIVE INGREDIENTS: SORBITOL; Water

ACTIVE INGREDIENT

Active ingredients: Silica 13.00%, Alcloxa 0.16%

INACTIVE INGREDIENT

Inactive ingredients:

Sorbitol, Water, Glycerin, Sodium Cocoyl Glutamate, Stevioside, Flavor, Cellulose Gum, Xylitol, Charcoal Powder, Glycyrrhiza Glabra (Licorice) Root Extract, Aloe Barbadensis Leaf Extract, Gentiana Lutea Root Extract, Lavandula Angustifolia (Lavender) Flower Extract, Camellia Sinensis Leaf Extract, Rosmarinus Officinalis (Rosemary) Leaf Extract, Salvia Officinalis (Sage) Leaf Extract, Chitosan, Chamomilla Recutita (Matricaria) Flower Extract, Propolis Extract, Scutellaria Baicalensis Root Extract, Mika, Commiphora Myrrha Oil, Krameria Triandra Root Extract, Chamaecyparis Obtusa Oil, Eucalyptus Globulus Leaf Oil

PURPOSE

Purpose: Anticavity

WARNINGS

If you accidentally swallow more than used for brushing, Seek professional help or contact a poison control center immediately.

KEEP OUT OF REACH OF CHILDREN

Uses

Aids in the prevention of cavities, plaque, and gingivitis.

Directions

children 2 yrs. older: Brush teeth thoroughly after meals or at least twice a day, or use as directed by a dentist or physician.: To minimize swallowing, use a pea-sized amount and supervise brushing until good habits are established. Children under 2 yrs.: Ask a dentist or physician